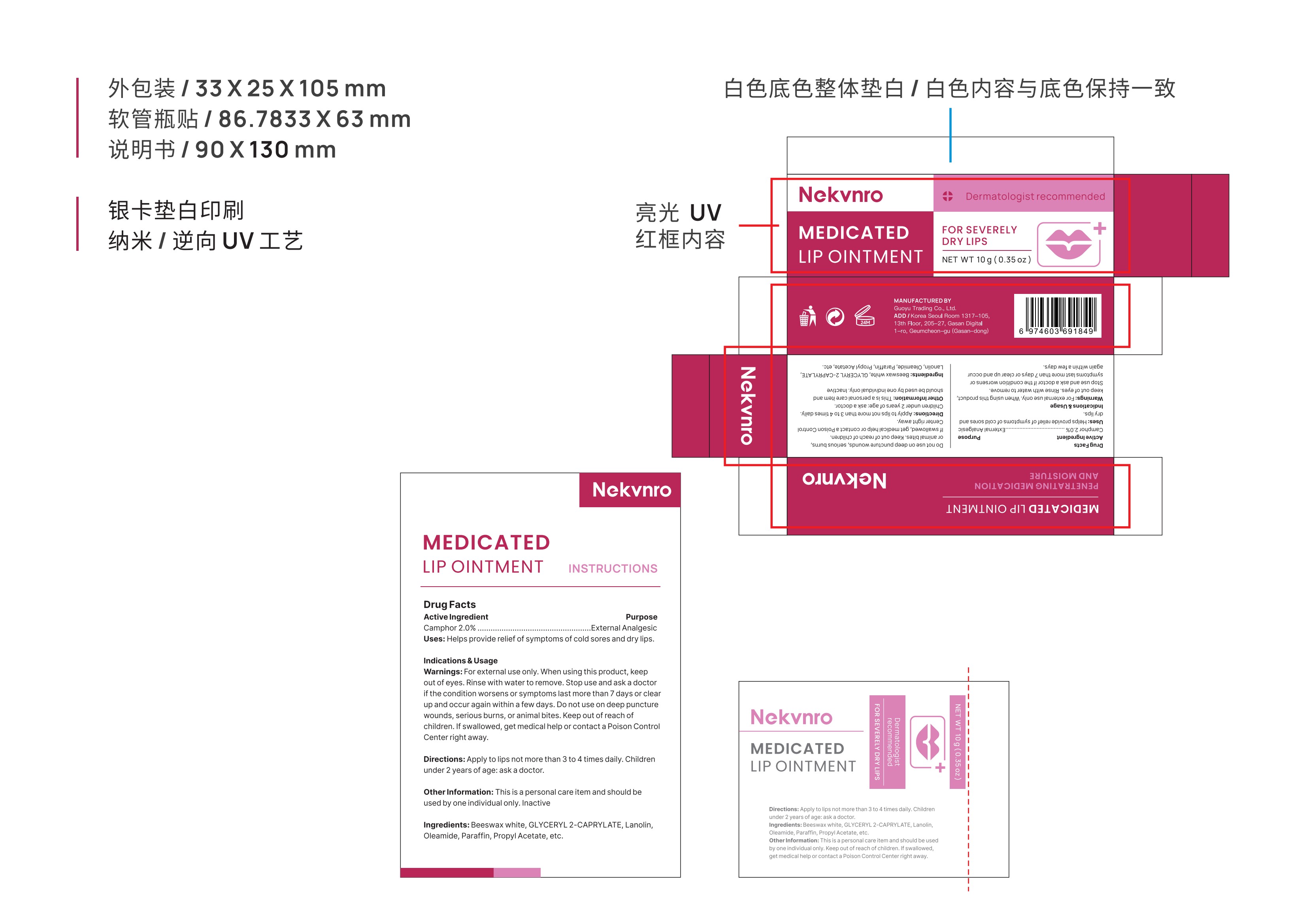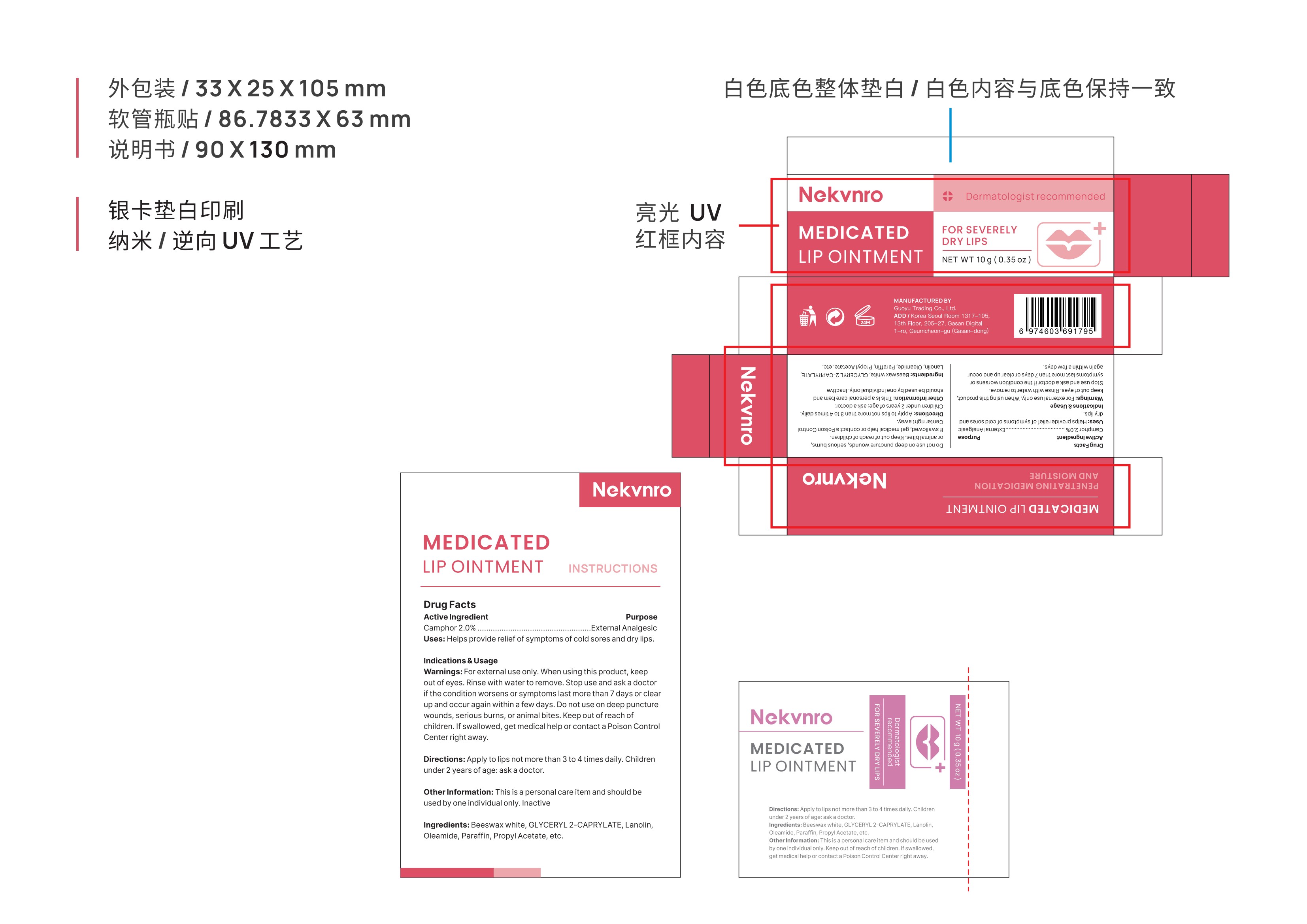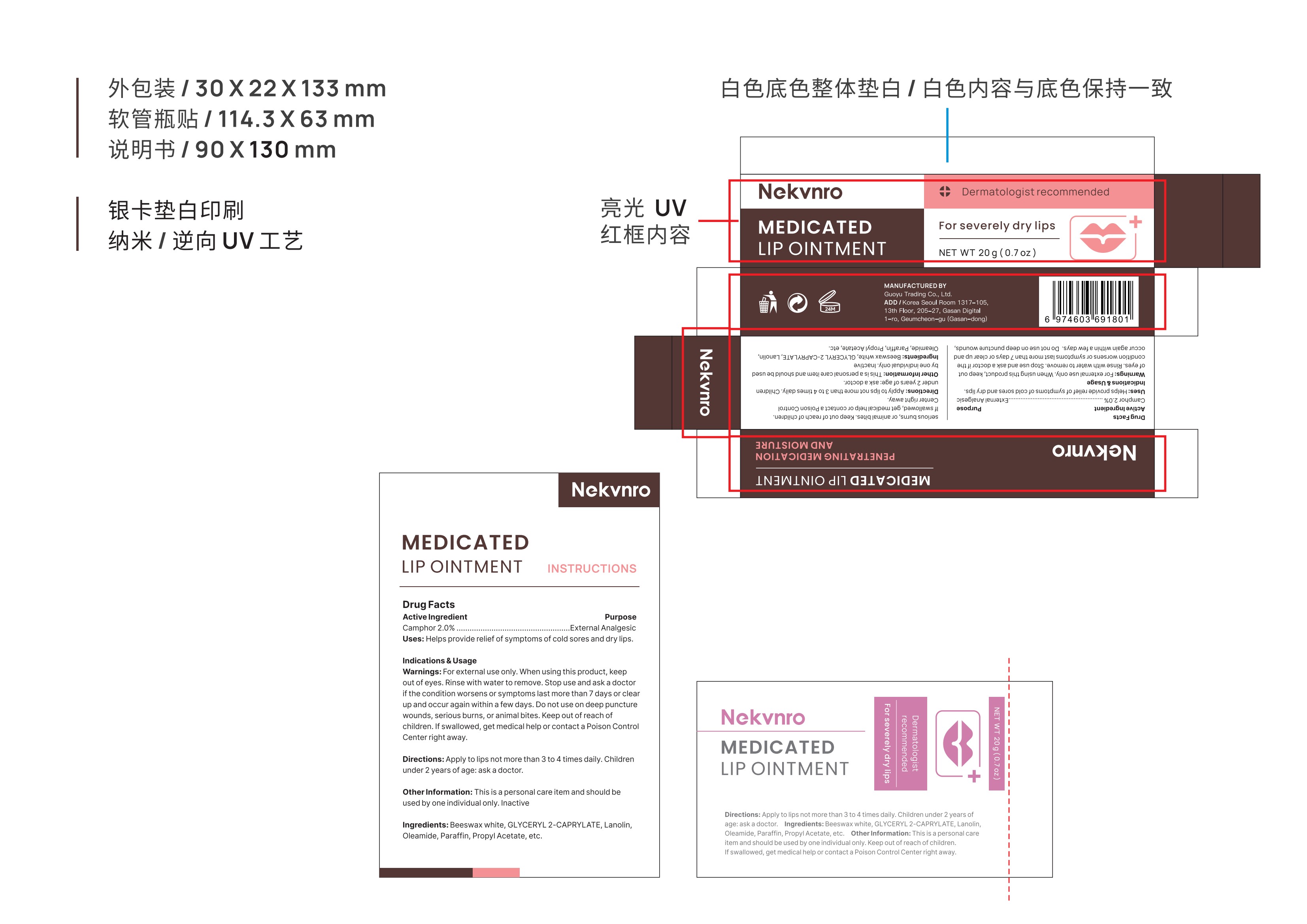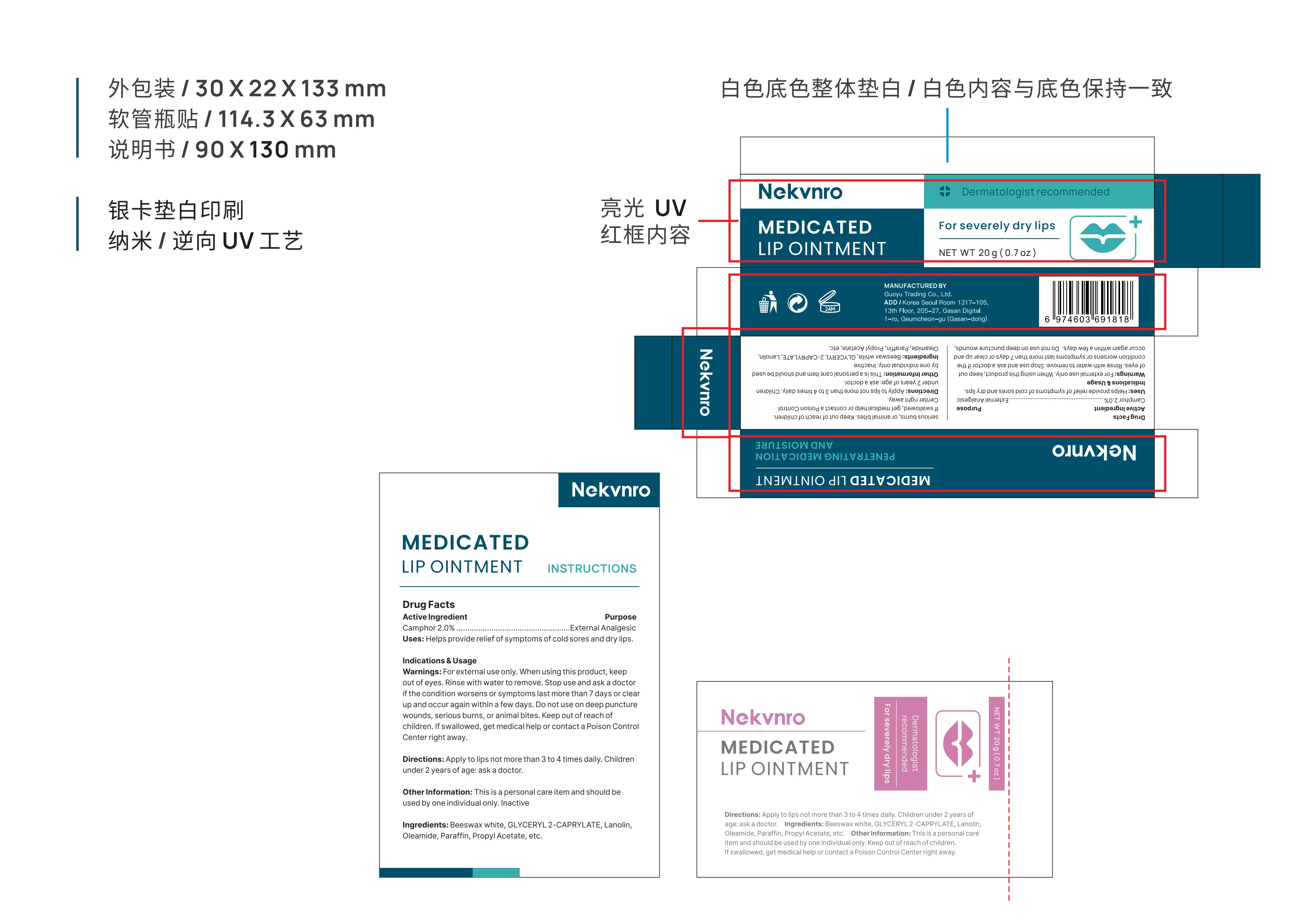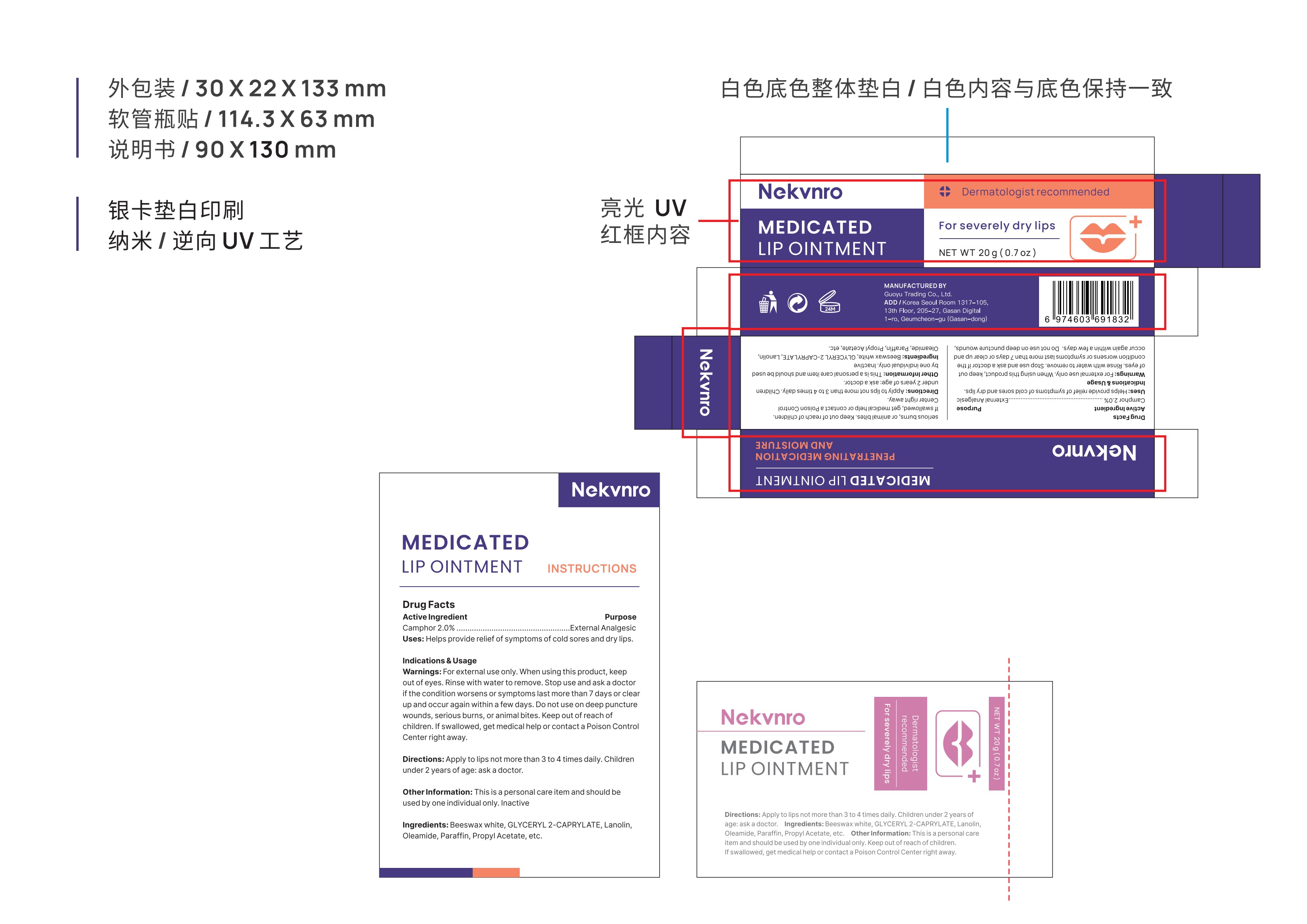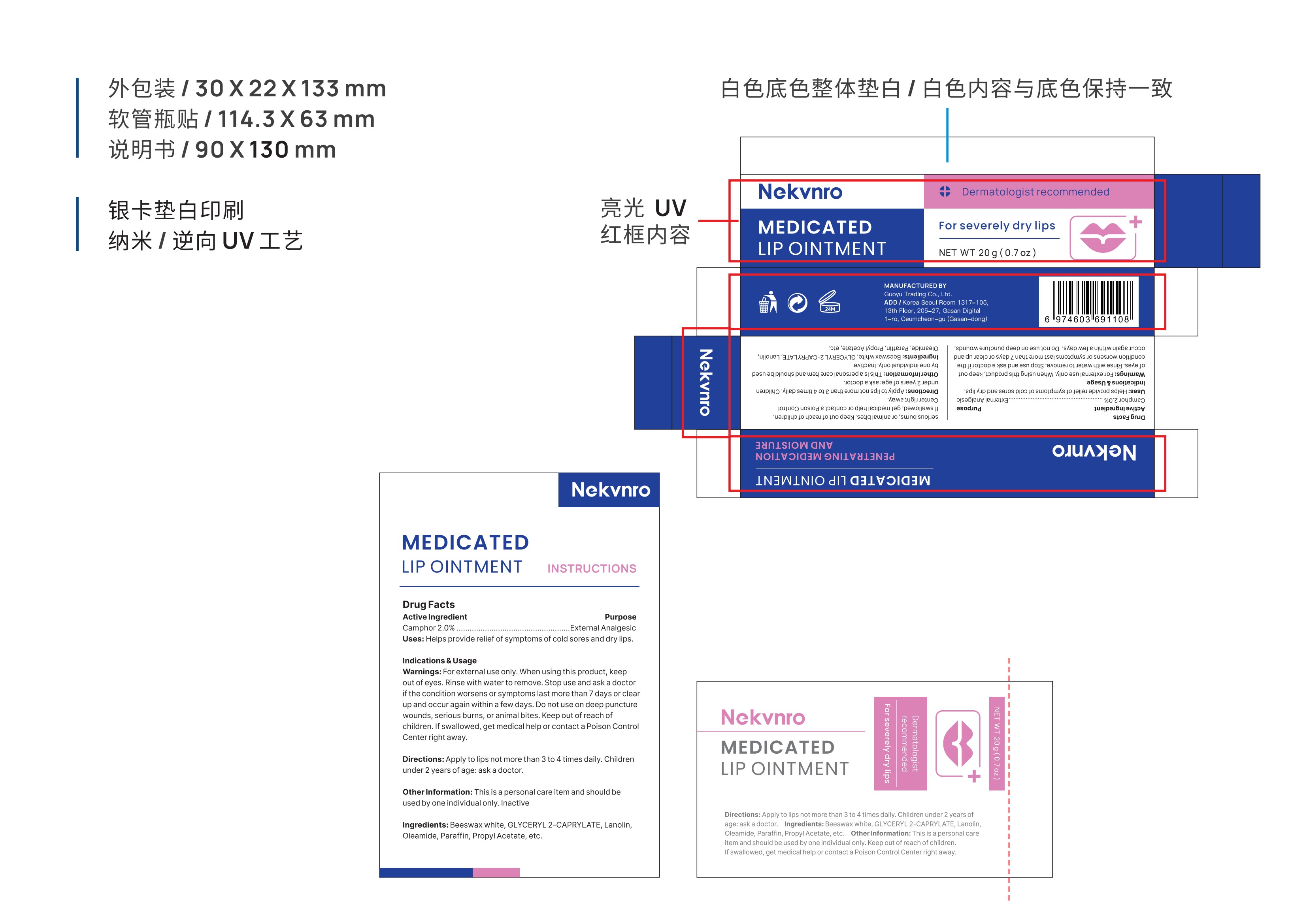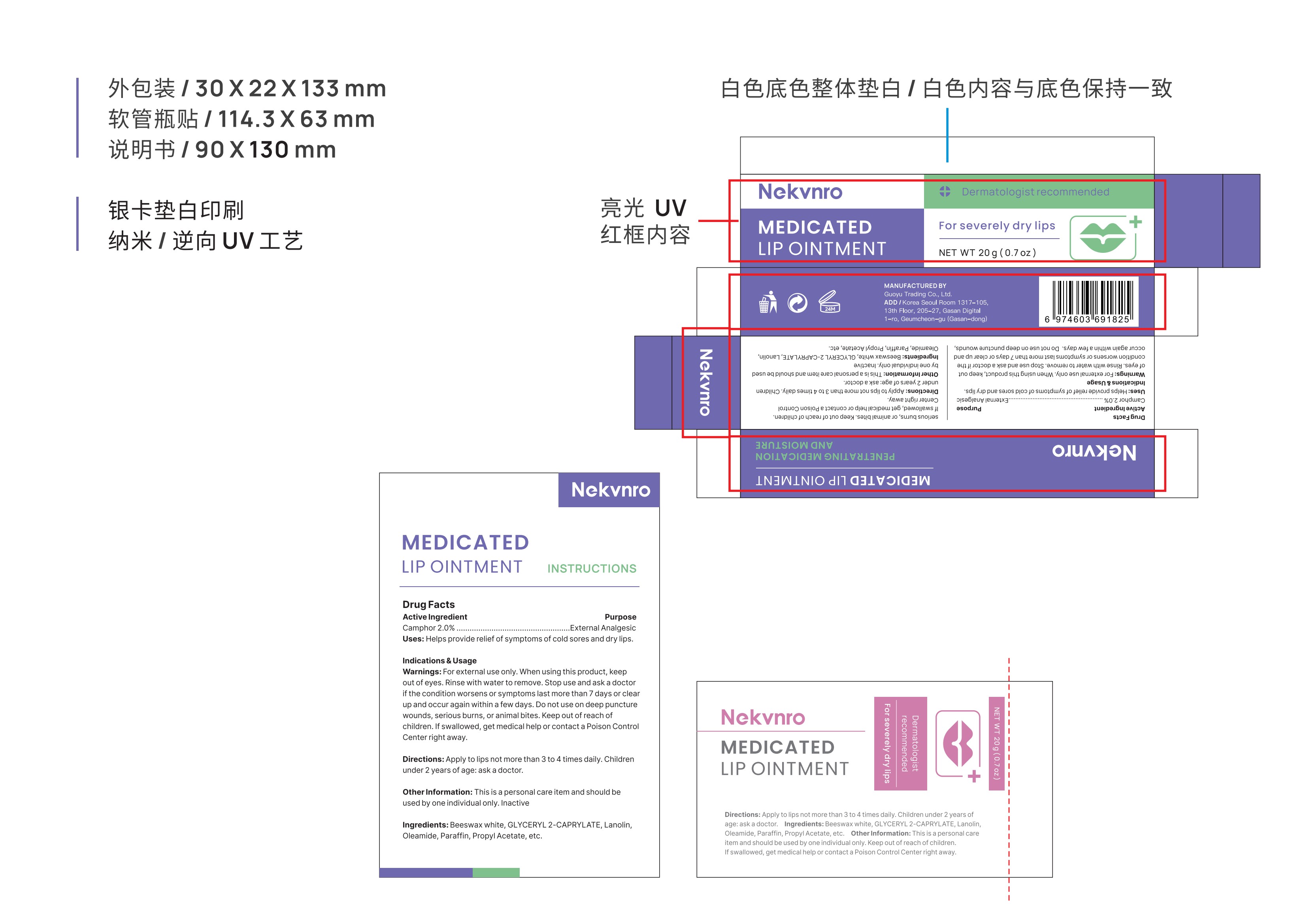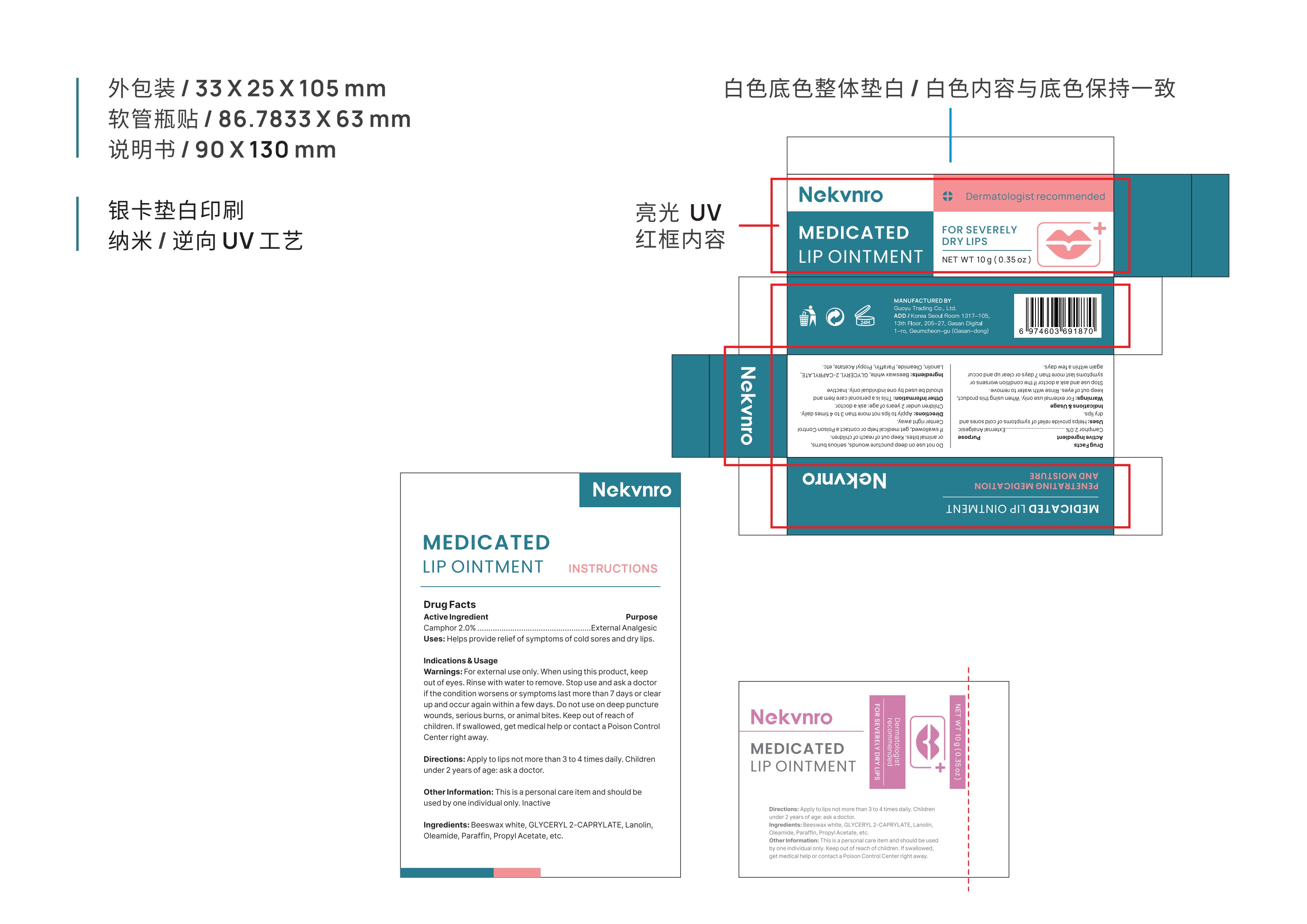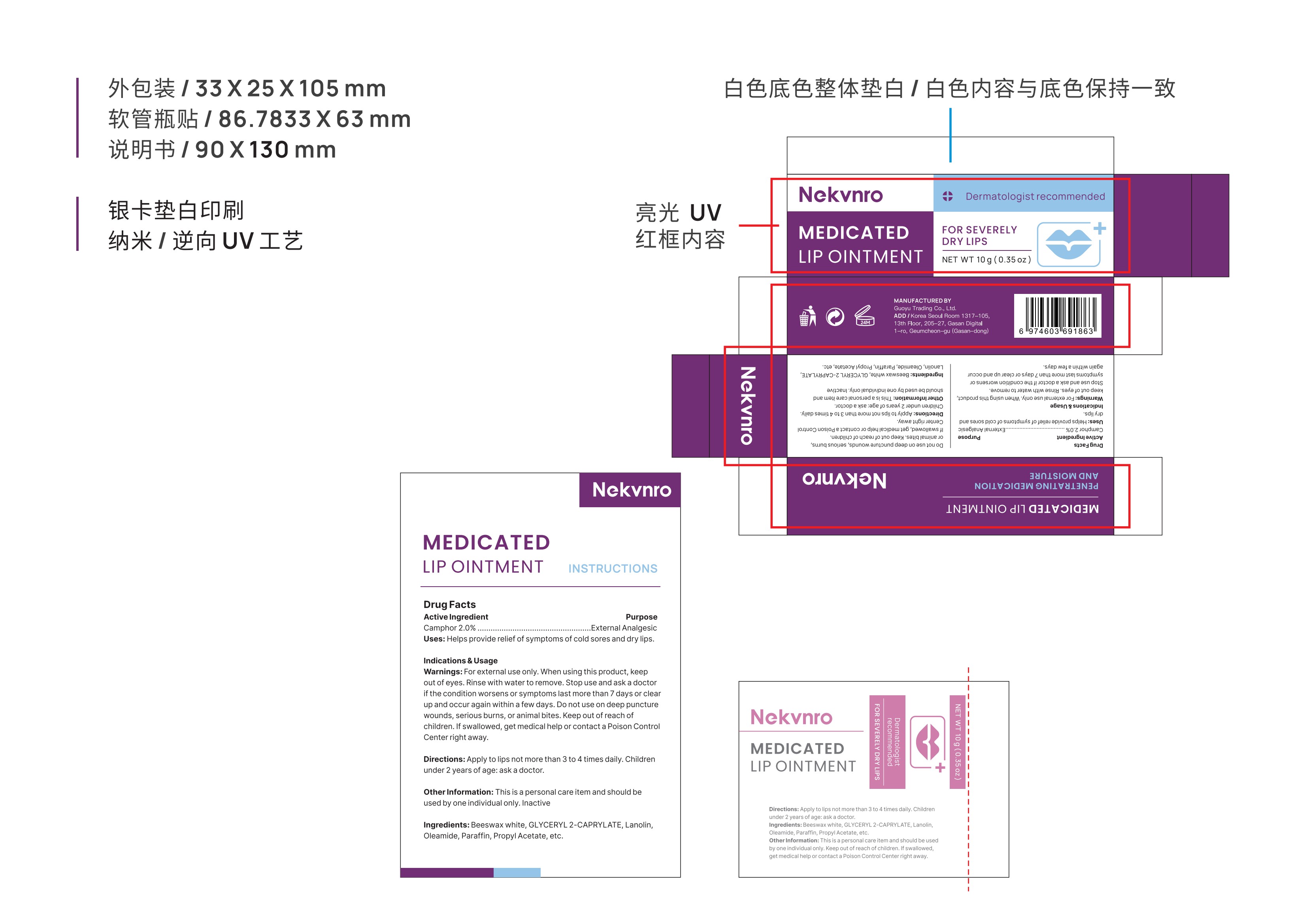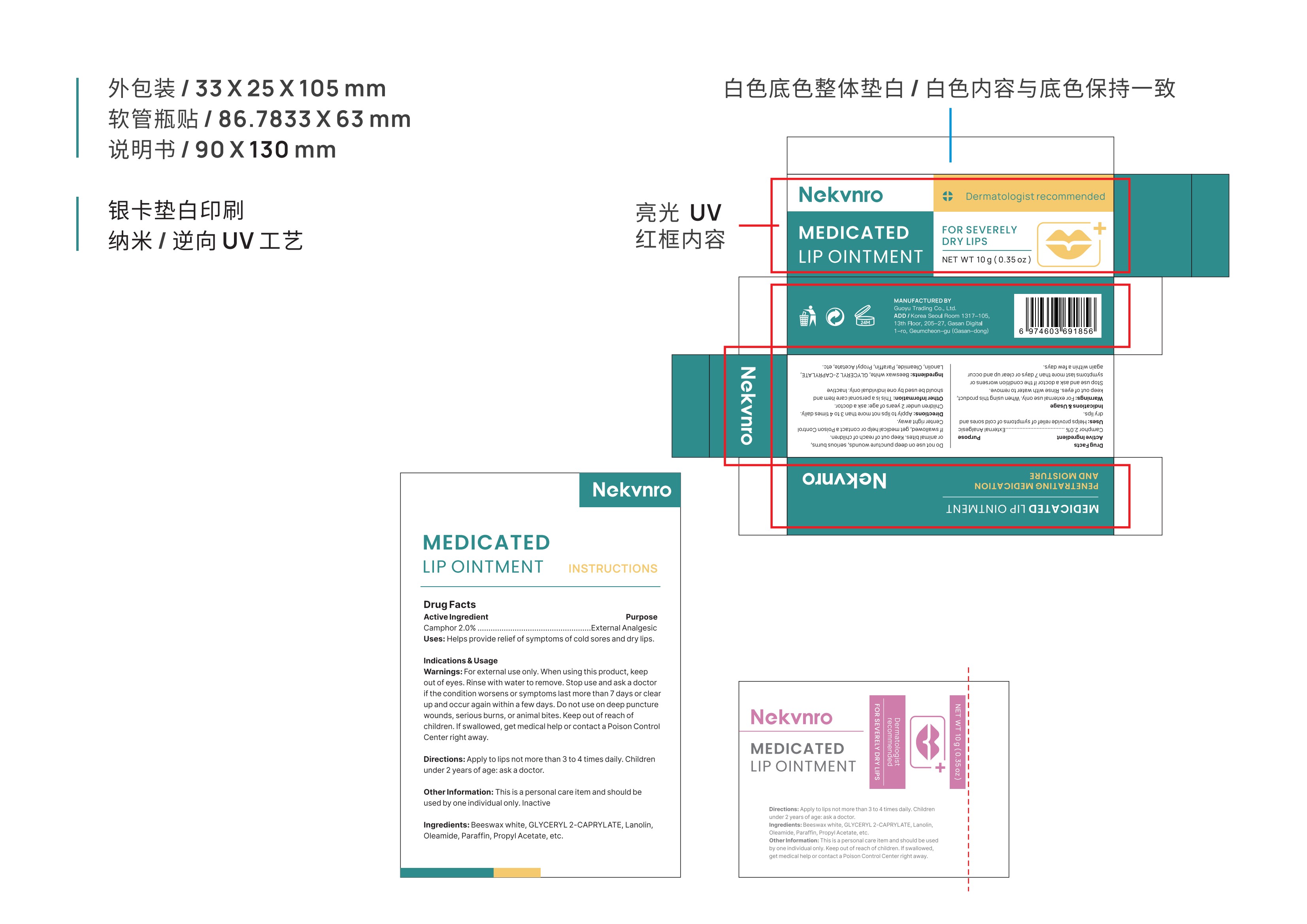 DRUG LABEL: Nekvnro Medicated Lip Ointment.
NDC: 84844-004 | Form: OINTMENT
Manufacturer: Guoyu Trading Co., Ltd.
Category: otc | Type: HUMAN OTC DRUG LABEL
Date: 20241030

ACTIVE INGREDIENTS: CAMPHOR (SYNTHETIC) 2 g/100 g
INACTIVE INGREDIENTS: LANOLIN; PROPYL ACETATE; PARAFFIN; WHITE WAX; GLYCERYL 2-CAPRYLATE; OLEAMIDE

84844-004

Active Ingredient

Camphor 2%

Purpose

External Analgesic

Use

·Helps provide relief of symptoms of cold sores and dry lips.

Warnings

·For external use only. When using this product, keep out of eyes. Rinse with water to remove.

Do not use

on deep puncture wounds, serious burns, or animal bites.

When Using

this product, keep out of eyes. Rinse with water to remove.

Stop Use

if the condition worsens or symptoms last more than 7 days or clear up and occur again within a few days

Ask Doctor

if the condition worsens or symptoms last more than 7 days or clear up and occur again within a few days

Keep Oot Of Reach Of Children

If swallowed, get medical help or contact a Poison Control Center right away.

Directions

· Apply to lips not more than 3 to 4 times daily. Children under 2 years of age: ask a doctor.

Other information

This is a personal care item and should be used by one individual only.Inactive

Inactive ingredients

·Beeswax white, GLYCERYL 2-CAPRYLATE，Lanolin, Oleamide, Paraffin,Propyl Acetate